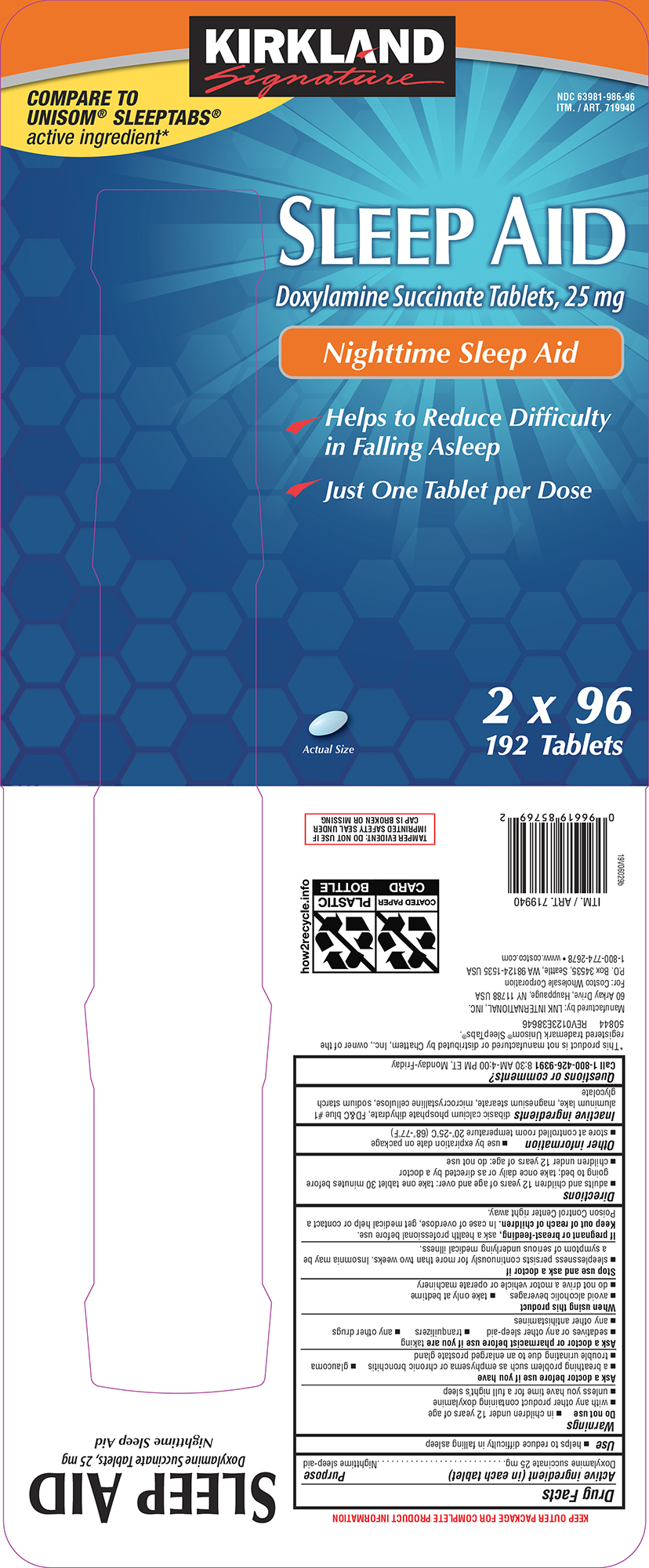 DRUG LABEL: Sleep Aid
NDC: 63981-986 | Form: TABLET
Manufacturer: COSTCO WHOLESALE CORPORATION
Category: otc | Type: HUMAN OTC DRUG LABEL
Date: 20250819

ACTIVE INGREDIENTS: DOXYLAMINE SUCCINATE 25 mg/1 1
INACTIVE INGREDIENTS: DIBASIC CALCIUM PHOSPHATE DIHYDRATE; FD&C BLUE NO. 1 ALUMINUM LAKE; MAGNESIUM STEARATE; MICROCRYSTALLINE CELLULOSE; SODIUM STARCH GLYCOLATE TYPE A POTATO

Kirkland 44-386

Active ingredient (in each tablet)

Doxylamine succinate 25 mg

Purpose

Nighttime sleep-aid

Use

- helps to reduce difficulty in falling asleep

Warnings

Do not use

- in children under 12 years of age
- with any other product containing doxylamine
- unless you have time for a full night’s sleep

Ask a doctor before use if you have

- a breathing problem such as emphysema or chronic bronchitis
- glaucoma
- trouble urinating due to an enlarged prostate gland

Ask a doctor or pharmacist before use if you are

taking

- sedatives or any other sleep-aid
- tranquilizers
- any other drugs
- any other antihistamines

When using this product

- avoid alcoholic beverages
- take only at bedtime
- do not drive a motor vehicle or operate machinery

Stop use and ask a doctor if

- sleeplessness persists continuously for more than two weeks. Insomnia may be a symptom of serious underlying medical illness.

If pregnant or breast-feeding,

ask a health professional before use.

Keep out of reach of children.

In case of overdose, get medical help or contact a Poison Control Center right away.

Directions

- adults and children 12 years of age and over: take one tablet 30 minutes before going to bed; take once daily or as directed by a doctor
- children under 12 years of age: do not use

Other information

- use by expiration date on package
- store at controlled room temperature 20°-25°C (68°-77°F)

Inactive ingredients

dibasic calcium phosphate dihydrate, FD&C blue #1 aluminum lake, magnesium stearate, microcrystalline cellulose, sodium starch glycolate

Questions or comments?

Call 1-800-426-9391 8:30 AM-4:00 PM ET, Monday-Friday

Principal display panel

KIRKLAND
Signature

COMPARE TO
UNISOM® SLEEPTABS®
active ingredient*

NDC 63981-986-96
ITM. / ART. 719940

SLEEP AID
Doxylamine Succinate Tablets, 25 mg
Nighttime Sleep Aid

Helps to Reduce Difficulty
in Falling Asleep

Just One Tablet per Dose

2 x 96
192 Tablets

Actual Size

TAMPER EVIDENT: DO NOT USE IF
IMPRINTED SAFETY SEAL UNDER
CAP IS BROKEN OR MISSING

*This product is not manufactured or distributed by Chattem, Inc., owner of the
registered trademark Unisom® SleepTabs®.
50844 REV0123E38646

Manufactured by: LNK INTERNATIONAL, INC.
60 Arkay Drive, Hauppauge, NY 11788 USA
For: Costco Wholesale Corporation
P.O. Box 34535, Seattle, WA 98124-1535 USA
1-800-774-2678 • www.costco.com

Kirkland 44-386